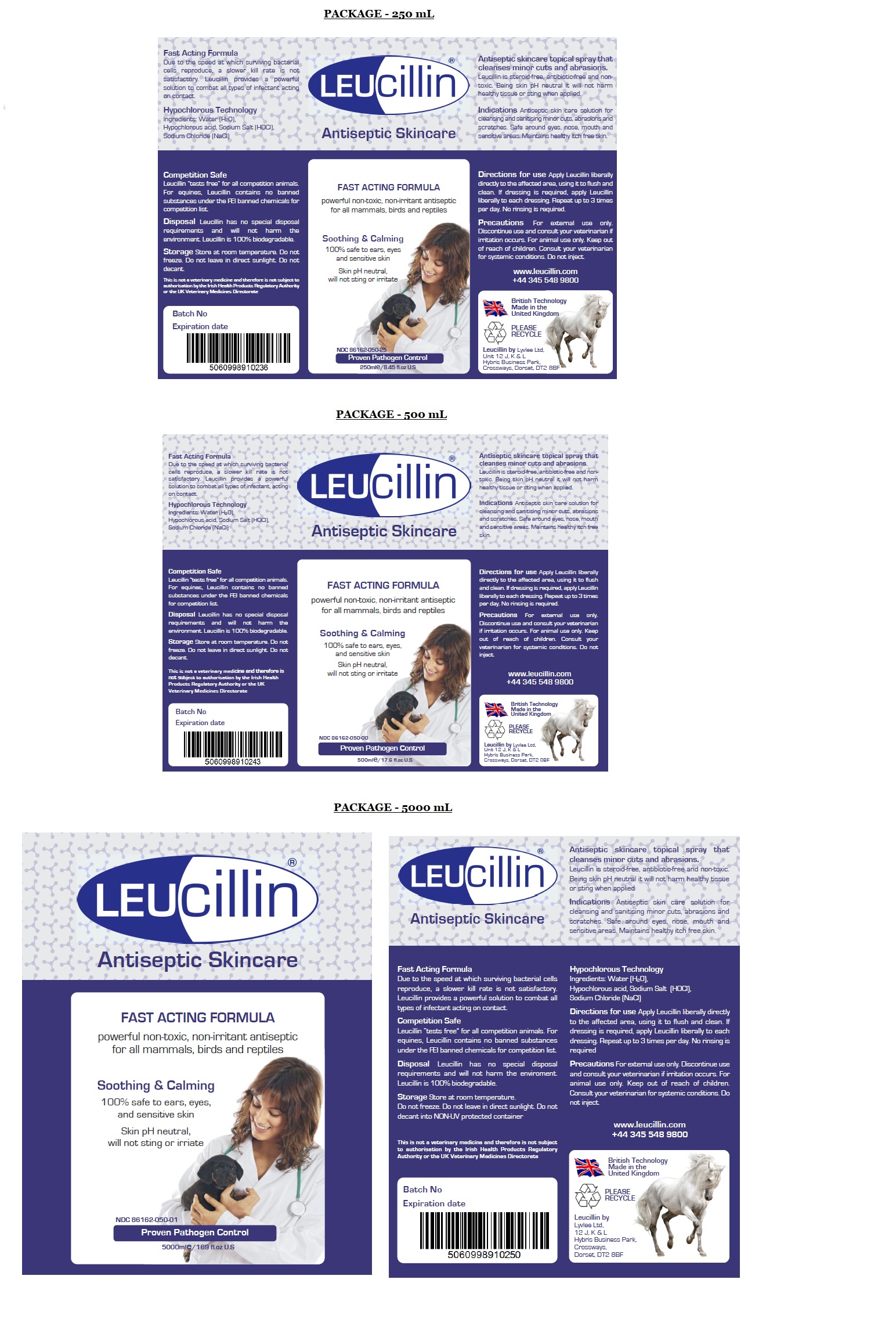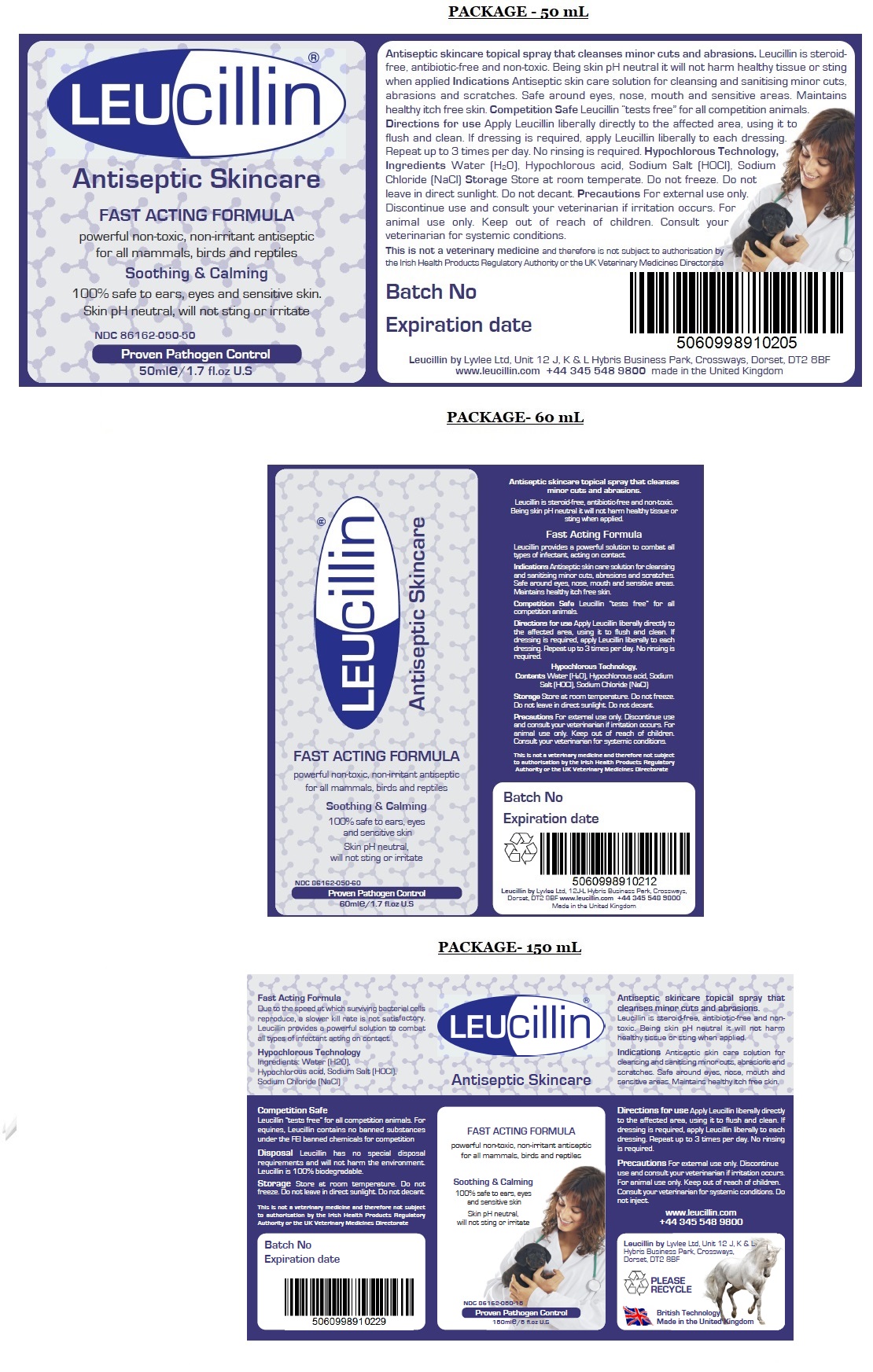 DRUG LABEL: Leucillin
NDC: 86162-050 | Form: LIQUID
Manufacturer: LYVLEE LIMITED
Category: animal | Type: OTC ANIMAL DRUG LABEL
Date: 20230405

ACTIVE INGREDIENTS: HYPOCHLOROUS ACID 0.03 g/100 mL
INACTIVE INGREDIENTS: WATER; SODIUM HYPOCHLORITE; SODIUM CHLORIDE

LEUcillin®

Antiseptic skincare topical spray that cleanses minor cuts and abrasions. Leucillin is steroid- free, antibiotic-free and non-toxic. Being skin pH neutral it will not harm healthy tissue or sting when applied

Indications

Antiseptic skin care solution for cleansing and sanitising minor cuts, abrasions and scratches. Safe around eyes, nose, mouth and sensitive areas. Maintains healthy itch free skin.

Directions for use

Apply Leucillin liberally directly to the affected area, using it to flush and clean. If dressing is required, apply Leucillin liberally to each dressing. Repeat up to 3 times per day. No rinsing is required.

Precautions

For external use only. Discontinue use and consult your veterinarian if irritation occurs. For animal use only. Keep out of reach of children. Consult your veterinarian for systemic conditions. Do not inject.

Hypochlorous Technology, Ingredients

Hypochlorous acid

Ingredients:

Water (H20), Sodium Salt (HOCl), Sodium Chloride (NaCl)

Storage

Store at room temperature. Do not freeze. Do not leave in direct sunlight. Do not decant.

Antiseptic Skincare

FAST ACTING FORMULA

powerful non-toxic, non-irritant antiseptic for all mammals, birds and reptiles

Soothing & Calming

100% safe to ears, eyes, and sensitive skin

Skin pH neutral, will not sting or irritate

Proven Pathogen Control

Leucillin by Lyvlee Ltd, Unit 12 J, K & L Hybris Business Park, Crossways, Dorset, DT2 8BF
www.leucillin.com +44 345 548 9800

info@leucillin.co.uk

British Technology
Made in the United Kingdom

Due to the speed at which surviving bacterial cells reproduce, a slower kill rate is not satisfactory. Leucillin provides a powerful solution to combat all types of infection acting on contact.

Competition Safe
Leucillin “tests free” for all competition animals. For equines, Leucillin contains no banned substances under the FEI banned chemicals for competition list.

Disposal Leucillin has no special disposal requirements and will not harm the environment. Leucillin is 100% biodegradable.

This is not a veterinary medicine and therefore not subject to authorisation by the Irish Health Products Regulatory Authority or the UK Veterinary Medicines Directorate